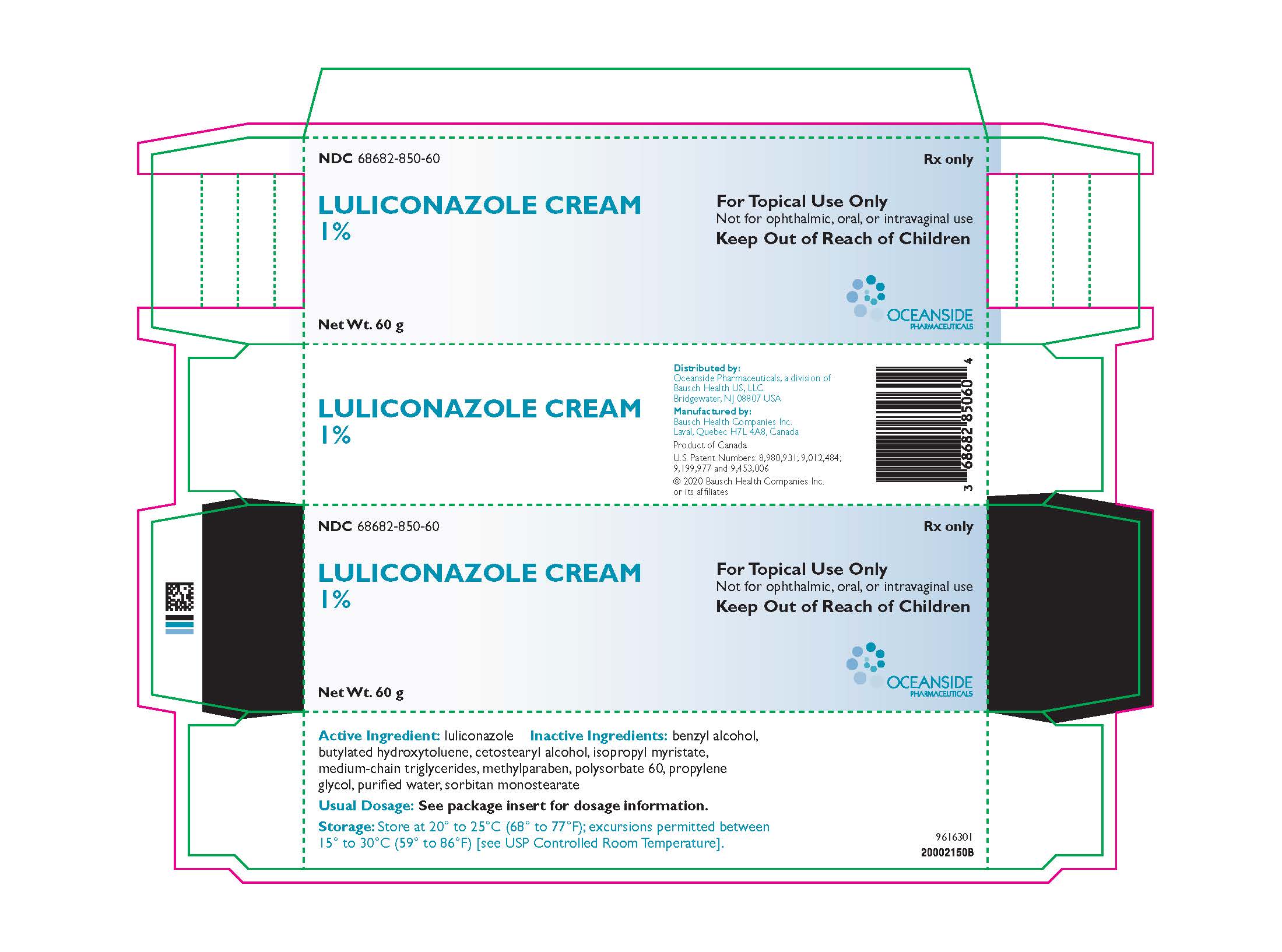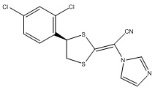 DRUG LABEL: LULICONAZOLE
NDC: 68682-850 | Form: CREAM
Manufacturer: Oceanside Pharmaceuticals
Category: prescription | Type: HUMAN PRESCRIPTION DRUG LABEL
Date: 20200430

ACTIVE INGREDIENTS: LULICONAZOLE 10 mg/1 g
INACTIVE INGREDIENTS: BENZYL ALCOHOL; BUTYLATED HYDROXYTOLUENE; CETOSTEARYL ALCOHOL; ISOPROPYL MYRISTATE; MEDIUM-CHAIN TRIGLYCERIDES; METHYLPARABEN; POLYSORBATE 60; PROPYLENE GLYCOL; WATER; SORBITAN MONOSTEARATE

HIGHLIGHTS OF PRESCRIBING INFORMATION

These highlights do not include all the information needed to use Luliconazole Cream safely and effectively. See full prescribing information for Luliconazole Cream.
Luliconazole cream, for topical use
Initial U.S. Approval: 2013

1 INDICATIONS AND USAGE

Luliconazole Cream, 1% is an azole antifungal indicated for the topical treatment of interdigital tinea pedis, tinea cruris, and tinea corporis caused by the organisms Trichophyton rubrum and Epidermophyton floccosum. (1)

2 DOSAGE AND ADMINISTRATION

- For topical use only. Not for ophthalmic, oral, or intravaginal use. (2)
- Interdigital Tinea Pedis: Luliconazole Cream, 1% should be applied to the affected and immediate surrounding area(s) once a day for 2 weeks. (2)
- Tinea Cruris and Tinea Corporis: Luliconazole Cream, 1% should be applied to the affected skin and immediate surrounding area(s) once a day for 1 week. (2)

3 DOSAGE FORMS AND STRENGTHS

Cream, 1% (3)

4 CONTRAINDICATIONS

None. (4)

6 ADVERSE REACTIONS

The most common adverse reactions observed in clinical trials were application site reactions, which occurred in less than 1% of subjects. (6.1)

To report SUSPECTED ADVERSE REACTIONS, contact Oceanside Pharmaceuticals at 1-800-321-4576 or FDA at 1-800-FDA-1088 or www.fda.gov/medwatch.

FULL PRESCRIBING INFORMATION

1 INDICATIONS AND USAGE

Luliconazole Cream, 1% is indicated for the topical treatment of interdigital tinea pedis, tinea cruris, and tinea corporis caused by the organisms Trichophyton rubrum and Epidermophyton floccosum.

2 DOSAGE AND ADMINISTRATION

For topical use only. Luliconazole Cream, 1% is not for ophthalmic, oral, or intravaginal use.

- When treating interdigital tinea pedis, a thin layer of Luliconazole Cream, 1% should be applied to the affected area and approximately 1 inch of the immediate surrounding area(s) once daily for 2 weeks.
- When treating tinea cruris or tinea corporis, Luliconazole Cream, 1% should be applied to the affected area and approximately 1 inch of the immediate surrounding area(s) once daily for 1 week.

3 DOSAGE FORMS AND STRENGTHS

Cream, 1%. Each gram of Luliconazole Cream, 1% contains 10 mg of luliconazole in a white cream base.

4 CONTRAINDICATIONS

None.

6 ADVERSE REACTIONS

6.1 Clinical Trials Experience

Because clinical trials are conducted under widely varying conditions, adverse reaction rates observed in the clinical trials of a drug cannot be directly compared to rates in the clinical trials of another drug and may not reflect the rates observed in practice.

In three Phase 3 clinical trials, 616 subjects were exposed to Luliconazole Cream, 1%: 305 with interdigital tinea pedis and 311 subjects with tinea cruris. Subjects with interdigital tinea pedis or tinea cruris applied Luliconazole Cream, 1% or vehicle cream once daily for 14 days or 7 days, respectively, to affected and adjacent areas. During clinical trials with Luliconazole Cream, 1%, the most common adverse reactions were application site reactions which occurred in less than 1% of subjects in both the Luliconazole and vehicle arms. Most adverse reactions were mild in severity.

A post-approval clinical trial was conducted in 75 subjects age 2 to <18 years old with tinea corporis. The adverse reactions in the Luliconazole Cream, 1% treated population were similar to the vehicle treated population.

6.2 Postmarketing Experience

The following adverse reactions have been identified during postmarketing use of luliconazole cream, 1%: contact dermatitis and cellulitis. Because these reactions are reported voluntarily from a population of uncertain size, it is not always possible to reliably estimate their frequency or establish a causal relationship to drug exposure.

7 DRUG INTERACTIONS

An in vivo study in adult subjects with moderate to severe interdigital tinea pedis and tinea cruris showed that Luliconazole Cream, 1% is mostly a weak inhibitor of CYP2C19. In a separate trial in adolescent subjects with tinea cruris, in vivo blood levels of Luliconazole Cream, 1%, were seen to approach those levels sufficient to show moderate inhibition of CYP2C19 [see Clinical Pharmacology (12.3)].

8 USE IN SPECIFIC POPULATIONS

8.1 Pregnancy

TERATOGENIC EFFECTS

Risk Summary

There are no available data with Luliconazole Cream, 1% use in pregnant women to inform a drug-associated risk for major birth defects and miscarriage. In animal reproduction studies with pregnant rats and rabbits, there were no adverse developmental effects observed with subcutaneous administration of luliconazole during organogenesis at doses up to 3 and 24 times, respectively, the maximum recommended human dose (MRHD) [see Data].

The background risk of major birth defects and miscarriage for the indicated population is unknown. All pregnancies have a background risk of birth defect, loss, or other adverse outcomes. In the U.S. general population, the estimated background risk of major birth defects and miscarriage in clinically recognized pregnancies is 2 to 4% and 15 to 20%, respectively.

Data

Animal Data

The animal multiples of human exposure calculations were based on daily dose body surface area (BSA) comparisons (mg/m^2) for the reproductive toxicology studies described in this section and in Section 13.1. The maximum recommended human dose (MRHD) was set at 8 g 1% cream per day (1.33 mg/kg/day for a 60 kg individual, which is equivalent to 49.2 mg/m^2/day).

Systemic embryofetal development studies were conducted in rats and rabbits. Subcutaneous doses of 1, 5 and 25 mg/kg/day luliconazole were administered during the period of organogenesis (gestational days 7-17) to pregnant female rats. No treatment-related effects on maternal toxicity or malformations were noted at 25 mg/kg/day (3 times the MRHD based on BSA comparisons). Increased incidences of skeletal variation (14th rib) were noted at 25 mg/kg/day. No treatment-related effects on skeletal variation were noted at 5 mg/kg/day (0.6 times the MRHD based on BSA comparisons).

Subcutaneous doses of 4, 20 and 100 mg/kg/day luliconazole were administered during the period of organogenesis (gestational days 6-18) to pregnant female rabbits. No treatment-related effects on maternal toxicity, embryofetal toxicity or malformations were noted at 100 mg/kg/day (24 times the MRHD based on BSA comparisons).

In a pre- and postnatal development study in rats, subcutaneous doses of 1, 5 and 25 mg/kg/day luliconazole were administered from the beginning of organogenesis (gestation day 7) through the end of lactation (lactation day 20). In the presence of maternal toxicity, embryofetal toxicity (increased prenatal pup mortality, reduced live litter sizes and increased postnatal pup mortality) was noted at 25 mg/kg/day.

No embryofetal toxicity was noted at 5 mg/kg/day (0.6 times the MRHD based on BSA comparisons). No treatment effects on postnatal development were noted at 25 mg/kg/day (3 times the MRHD based on BSA comparisons).

8.2 Lactation

Risk Summary

There is no information available on the presence of luliconazole in human milk, the effects of the drug on the breastfed infant, or the effects of the drug on milk production after topical application of Luliconazole Cream, 1% to women who are breastfeeding. Luliconazole Cream, 1% has low systemic absorption. The lack of clinical data during lactation precludes a clear determination of the risk of Luliconazole Cream, 1% to an infant during lactation. Therefore, the developmental and health benefits of breastfeeding should be considered along with the mother’s clinical need for Luliconazole Cream, 1% and any potential adverse effects on the breastfed infant from Luliconazole Cream, 1% or from the underlying maternal condition.

8.4 Pediatric Use

The safety and effectiveness of Luliconazole Cream, 1% in pediatric patients 12 to <18 years of age with tinea pedis and tinea cruris have been established by evidence from well-controlled trials in adult and pediatric subjects and a pharmacokinetic (PK) study in pediatric subjects [see Clinical Pharmacology (12.3) and Clinical Studies (14)].

The safety and effectiveness of Luliconazole Cream, 1% in pediatric patients 2 to <18 years of age with tinea corporis have been established by evidence from a well-controlled trial in pediatric subjects [see Clinical Pharmacology (12.3) and Clinical Studies (14)].

8.5 Geriatric Use

Of the total number of subjects in clinical studies of Luliconazole Cream, 1%, 8% were 65 and over, while 1.4% were 75 and over. No overall differences in safety or effectiveness were observed between these subjects and younger subjects, and other reported clinical experience has not identified differences in responses between the elderly and younger patients, but greater sensitivity of some older individuals cannot be ruled out.

11 DESCRIPTION

Luliconazole Cream, 1% contains 1% luliconazole, an azole antifungal agent, in a white cream for topical application.

Luliconazole is (2E)-2-[(4R)-4-(2,4-dichlorophenyl)-1,3-dithiolan-2-ylidene]-2-imidazol-1-ylacetonitrile. Its structural formula is:

The molecular formula is C14H9Cl2N3S2 with a molecular weight of 354.28. Luliconazole is the R enantiomer and contains one chiral center. The double bond adjacent to the dithiolane group is in the E configuration.

Luliconazole Cream, 1% contains 10 mg of luliconazole per gram of cream in a vehicle consisting of benzyl alcohol, butylated hydroxytoluene, cetostearyl alcohol, isopropyl myristate, medium-chain triglycerides, methylparaben, polysorbate 60, propylene glycol, purified water, and sorbitan monostearate.

12 CLINICAL PHARMACOLOGY

12.1 Mechanism of Action

Luliconazole Cream, 1% is an azole antifungal [see Microbiology (12.4)].

12.2 Pharmacodynamics

At therapeutic doses, Luliconazole Cream, 1% is not expected to prolong QTc to any clinically relevant extent.

12.3 Pharmacokinetics

Luliconazole is the R enantiomer of a chiral molecule. The potential for interconversion between R and S enantiomers in humans has not been assessed. Information on the pharmacokinetics of luliconazole presented below refers to both R enantiomer and S enantiomer, if any, combined.

Luliconazole is >99% protein bound in plasma.

In a PK trial, 12 subjects with moderate to severe tinea pedis and 8 subjects with moderate to severe tinea cruris applied a mean daily amount of approximately 3.5 grams of Luliconazole Cream, 1% to the affected and surrounding areas once daily for 15 days. Plasma concentrations of luliconazole on Day 15 were measurable in all subjects and fluctuated little during the 24-hour interval. In subjects with tinea pedis, the mean ± SD of the maximum concentration (Cmax) was 0.40 ± 0.76 ng/mL after the first dose and 0.93 ± 1.23 ng/mL after the final dose. The mean time to reach Cmax (Tmax) was 16.9 ± 9.39 hours after the first dose and 5.8 ± 7.61 hours after the final dose. Exposure to luliconazole, as expressed by area under the concentration time curve (AUC0–24), was 6.88 ± 14.50 ng*hr/mL after the first dose and 18.74 ± 27.05 ng*hr/mL after the final dose. In subjects with tinea cruris, the mean ± SD Cmax was 4.91 ± 2.51 ng/mL after the first dose and 7.36 ± 2.66 ng/mL after the final dose. The mean Tmax was 21.0 ± 5.55 hours after the first dose and 6.5 ± 8.25 hours after the final dose. Exposure to luliconazole, as expressed by AUC0–24, was 85.1 ± 43.69 ng*hr/mL after the first dose and 121.74 ± 53.36 ng*hr/mL after the final dose.

PK data of luliconazole measured in adolescent subjects (12 to <18 years of age) with moderate to severe interdigital tinea pedis or moderate to severe tinea cruris as well as in subjects 2 to <18 years of age with tinea corporis are described in Specific Populations below.

Specific Populations

PK of luliconazole was assessed in 30 adolescent subjects 12 to <18 years of age with moderate to severe interdigital tinea pedis (N=15) or moderate to severe tinea cruris (N=15). Subjects with tinea pedis applied approximately 3 grams of Luliconazole Cream, 1% once daily to the affected area and adjacent skin for 15 days, while subjects with tinea cruris applied Luliconazole Cream, 1% once daily to the affected and adjacent skin for 8 days.

Generally, the systemic exposure of luliconazole was greater in the subjects with tinea cruris than tinea pedis. In subjects with tinea pedis, the systemic concentrations of luliconazole were quantifiable in all the subjects on Day 8 and Day 15. The mean ± SD Cmax was 1.80 ± 1.86 ng/mL after the first dose on Day 1, and 3.93 ± 1.67 ng/mL and 3.27 ± 1.71 ng/mL on Days 8 and 15, respectively. The mean ± SD AUC0-24 was 20.47 ± 14.47 ng*hr/mL after the first dose on Day 1, and 64.94 ± 32.47 ng*hr/mL and 60.38 ± 37.92 ng*hr/mL on Days 8 and Day 15, respectively. Like in adult subjects, the mean plasma concentrations of luliconazole in adolescent subjects on Days 8 and 15 were similar and fluctuated little during a 24-hour interval.

In subjects with moderate to severe tinea cruris, the systemic concentrations of luliconazole were quantifiable in all the subjects on Day 8. The mean ± SD Cmax was 9.80 ± 5.94 ng/mL after the first dose (Day 1) and 15.40 ± 13.62 ng/mL after the last dose (Day 8). The mean ± SD AUC0-24 was 157.07 ± 92.18 ng*hr/mL and 266.06 ± 236.07 ng*hr/mL, after the first dose (Day 1) and the last dose (Day 8).

In subjects with tinea corporis, the systemic concentrations of luliconazole were assessed at pre-dose and at 6 hours post-dose on the last day of treatment following once daily treatment with Luliconazole Cream, 1% for 7 days. The systemic concentrations were quantifiable in all the 12 subjects and the mean ± SD daily dose of Luliconazole Cream, 1% was 2.84 ± 1.82 g. The mean ± SD concentrations of luliconazole at 15 minutes prior to dosing and at 6 hours post-dose on Day 7 were 4.63 ± 2.93 ng/mL and 4.84 ± 3.33 ng/mL, respectively.

Drug Interactions

Results of in vitro studies indicated that therapeutic doses of Luliconazole Cream, 1% did not inhibit cytochrome P450 (CYP) enzymes 1A2, 2C9 and 2D6, but can inhibit the activity of CYP2B6, 2C8, 2C19, and 3A4. The most sensitive enzyme, CYP2C19, was further evaluated in an in vivo study using omeprazole as a probe substrate in adult subjects with moderate to severe interdigital tinea pedis and tinea cruris. The results showed that Luliconazole Cream, 1% applied at a daily amount of approximately 4 grams increased the omeprazole systemic exposure (AUC) by approximately 30% compared to the exposure of omeprazole administered alone. Luliconazole Cream, 1% is considered a weak inhibitor of CYP2C19.

For tinea cruris, extrapolation from both in vitro inhibition studies and in vivo data in adults to the adolescent subjects showed that in some subjects, levels of luliconazole can approach or exceed those required to be a moderate inhibitor of CYP2C19.

Results of in vitro studies indicated that therapeutic doses of Luliconazole Cream, 1% did not induce CYP1A2, 2B6, and 3A4.

12.4 Microbiology

Mechanism of Action

Luliconazole is an antifungal that belongs to the azole class. Although the exact mechanism of action against dermatophytes is unknown, luliconazole appears to inhibit ergosterol synthesis by inhibiting the enzyme lanosterol demethylase. Inhibition of this enzyme’s activity by azoles results in decreased amounts of ergosterol, a constituent of fungal cell membranes, and a corresponding accumulation of lanosterol.

Mechanism of Resistance

To date, a mechanism of resistance to luliconazole has not been described.

Luliconazole Cream, 1% has been shown to be active against most isolates of the following fungi, both in vitro and in clinical infections as described in the INDICATIONS AND USAGE section:

Trichophyton rubrum
Epidermophyton floccosum

13 NONCLINICAL TOXICOLOGY

13.1 Carcinogenesis, Mutagenesis, Impairment of Fertility

Long-term studies to evaluate the carcinogenic potential of Luliconazole Cream, 1% have not been conducted.

Luliconazole revealed no evidence of mutagenic or clastogenic potential based on the results of two in vitro genotoxicity tests (Ames assay and Chinese hamster lung cell chromosomal aberration assay) and one in vivo genotoxicity test (mouse bone marrow micronucleus test).

In a fertility study in rats, subcutaneous doses of 1, 5 and 25 mg/kg/day luliconazole were administered prior to and during mating and through early pregnancy. Treatment-related effects on reproductive function were noted in females (decreased live embryos and decreased corpus luteum) at 5 and 25 mg/kg/day and males (decreased sperm counts) at 25 mg/kg/day. No treatment-related effects on fertility or reproductive function were noted at 1 mg/kg/day (0.1× MRHD based on BSA comparisons).

14 CLINICAL STUDIES

14.1 Interdigital Tinea Pedis

The safety and efficacy of Luliconazole Cream, 1% was evaluated in two randomized, double-blind, vehicle-controlled, multi-center clinical trials in 423 subjects with a clinical and culture-confirmed diagnosis of interdigital tinea pedis. Subjects were randomized to receive Luliconazole Cream, 1% or vehicle. Subjects applied either Luliconazole Cream, 1% or vehicle cream to the entire area of the forefeet including all interdigital web spaces and approximately 2.5 cm (1 in) of the surrounding area of the foot once daily for 14 days.

The mean age of the study population was 41 years (range 13 to 78 years); 82% were male; 53% were White and 40% were Black or African American. Signs and symptoms of tinea pedis (erythema, scaling, and pruritus), KOH exam and dermatophyte culture were assessed at baseline, end-of-treatment (Day 14), 2 and 4 weeks post-treatment.

Overall treatment success was defined as complete clearance (clinical cure and mycological cure) at 4 weeks post-treatment. Luliconazole Cream, 1% demonstrated complete clearance in subjects with interdigital tinea pedis. Treatment outcomes at 4 weeks post-treatment are summarized in Table 1.

Table 1: Efficacy Results at 4 Weeks Post-treatment – Interdigital Tinea Pedis
 | Study 1 |  | Study 2
 | Luliconazole Cream, 1% N=106 n (%) | Vehicle Cream N=103 n (%) | Luliconazole Cream, 1% N=107 n (%) | Vehicle Cream N=107 n (%)
Complete Clearance [Proportion of subjects who achieved both clinical cure and mycological cure] | 28 (26%) | 2 (2%) | 15 (14%) | 3 (3%)
Effective Treatment [Negative KOH and culture and at most mild erythema and/or scaling and no pruritus] | 51 (48%) | 10 (10%) | 35 (33%) | 16 (15%)
Clinical Cure [Absence of erythema, scaling and pruritus] | 31 (29%) | 8 (8%) | 16 (15%) | 4 (4%)
Mycological Cure [Negative KOH and negative fungal culture] | 66 (62%) | 18 (18%) | 60 (56%) | 29 (27%)

14.2 Tinea Cruris

The safety and efficacy of Luliconazole Cream, 1% was evaluated in a randomized, double-blind, vehicle-controlled, multi-center clinical trial in 256 subjects with a clinical and culture-confirmed diagnosis of tinea cruris. Subjects were randomized to receive Luliconazole Cream, 1% or vehicle. Subjects applied either Luliconazole Cream, 1% or vehicle cream to the affected area and approximately 2.5 cm (1 in) of the surrounding area once daily for 7 days.

The mean age of the study population was 40 years (range 14 to 88 years); 83% were male; 58% were White and 34% were Black or African American. Signs and symptoms of tinea cruris (erythema, scaling, and pruritus), positive KOH exam and dermatophyte culture were assessed at baseline, end-of-treatment (Day 7), 2 and 3 weeks post-treatment.

Overall treatment success was defined as complete clearance (clinical cure and mycological cure) at 3 weeks post-treatment. Luliconazole Cream, 1% demonstrated complete clearance in subjects with tinea cruris. Treatment outcomes at 3 weeks post-treatment are summarized in Table 2.

Table 2: Efficacy Results at 3 Weeks Post-treatment - Tinea Cruris
 | Luliconazole Cream, 1% N=165 n (%) | Vehicle Cream N=91 n (%)
Complete Clearance [Proportion of subjects who achieved both clinical cure and mycological cure] | 35 (21%) | 4 (4%)
Effective Treatment [Negative KOH and culture and at most mild erythema and/or scaling and no pruritus] | 71 (43%) | 17 (19%)
Clinical Cure [Absence of erythema, scaling and pruritus] | 40 (24%) | 6 (7%)
Mycological Cure [Negative KOH and negative fungal culture] | 129 (78%) | 41 (45%)

14.3 Tinea Corporis

The safety and efficacy of Luliconazole Cream, 1% was evaluated in a randomized, double-blind, vehicle-controlled, multi-center clinical trial in 75 subjects age 2 to <18 years old with a clinical and culture-confirmed diagnosis of tinea corporis. Subjects were randomized to receive Luliconazole Cream, 1% or vehicle cream. Subjects applied either Luliconazole Cream, 1% or vehicle cream to the affected area and approximately 2.5 cm (1 in) of the surrounding skin once daily for 7 days.

The mean age of the study population was 8 years; 72% were male; 36% were White and 64% were Black or African American. Signs and symptoms of tinea cruris (erythema, scaling, and pruritus), positive KOH exam and dermatophyte culture were assessed at baseline, end-of-treatment (Day 7), 2 and 3 weeks post-treatment.

Treatment outcomes at 3 weeks post-treatment are summarized in Table 3.

Table 3: Efficacy Results at 3 Weeks Post-treatment - Tinea Corporis

Luliconazole Cream, 1%; N=51; n (%) | Vehicle Cream; N=14; n (%)
Complete Clearance [Proportion of subjects who achieved both clinical cure and mycological cure] | 36 (71%) | 5 (36%)
Effective Treatment [Negative KOH and culture and at most mild erythema and/or scaling and no pruritus] | 39 (77%) | 8 (57%)
Clinical Cure [Absence of erythema, scaling and pruritus] | 41 (80%) | 6 (43%)
Mycological Cure [Negative KOH and negative fungal culture] | 41 (80%) | 8 (57%)

16 HOW SUPPLIED/STORAGE AND HANDLING

Luliconazole Cream, 1% is a white cream supplied in tubes as follows:

60 g NDC 68682-850-60

STORAGE AND HANDLING

Store at 20° to 25°C (68° to 77°F); excursions permitted from 15° to 30°C (59° to 86°F) [see USP Controlled Room Temperature].

17 PATIENT COUNSELING INFORMATION

Advise the patient to read the FDA-approved patient labeling (Patient Information).

- Inform patients that Luliconazole Cream, 1% is for topical use only. Luliconazole Cream, 1% is not intended for intravaginal or ophthalmic use.

Distributed by:
Oceanside Pharmaceuticals, a division of
Bausch Health US, LLC
Bridgewater, NJ 08807 USA

Manufactured by:
Bausch Health Companies Inc.
Laval, Quebec H7L 4A8, Canada
U.S. Patent Numbers: 8,980,931; 9,012,484; 9,199,977 and 9,453,006

© 2020 Bausch Health Companies Inc. or its affiliates

9616403

PATIENT INFORMATION
Luliconazole Cream, 1%

Important information: Luliconazole Cream is for use on skin only. Do not get Luliconazole Cream near or in your eyes, mouth or vagina.

What is Luliconazole Cream?

Luliconazole Cream is a prescription medicine used on the skin (topical) to treat fungal infections in people with athlete's foot that is between the toes, jock itch, and ringworm.

Before using Luliconazole Cream, tell your doctor about all of your medical conditions, including if you:

- are pregnant or plan to become pregnant. It is not known if Luliconazole Cream will harm your unborn baby.
- are breastfeeding or plan to breastfeed. It is not known if Luliconazole Cream passes into your breast milk.

Tell your doctor about all of the medicines you take, including prescription and over-the-counter medicines, vitamins, and herbal supplements.

How should I use Luliconazole Cream?

- Use Luliconazole Cream exactly as your doctor tells you to use it.
- If you have athlete's foot between the toes, apply a thin layer of Luliconazole Cream to the affected skin areas and to about 1 inch of the surrounding skin 1 time a day for 2 weeks.
- If you have jock itch or ringworm, apply Luliconazole Cream to the affected skin areas and to about 1 inch of the surrounding skin 1 time a day for 1 week.
- Wash your hands after you apply Luliconazole Cream.

What are the possible side effects of Luliconazole Cream?

Luliconazole Cream may cause skin reactions at the treatment site. Skin irritation may happen with Luliconazole Cream. Tell your doctor if you have any skin reactions on the areas of your skin treated with Luliconazole Cream.

These are not all the possible side effects of Luliconazole Cream.

Call your doctor for medical advice about side effects. You may report side effects to FDA at 1-800-FDA-1088.

How should I store Luliconazole Cream?

- Store Luliconazole Cream at room temperature between 68°F to 77°F (20°C to 25°C).

Keep Luliconazole Cream and all medicines out of the reach of children.

General information about the safe and effective use of Luliconazole Cream

Medicines are sometimes prescribed for purposes other than those listed in a Patient Information leaflet. Do not use Luliconazole Cream for a condition for which it was not prescribed. Do not give Luliconazole Cream to other people, even if they have the same symptoms that you have. It may harm them. You can ask your pharmacist or doctor for information about Luliconazole Cream that is written for health professionals.

What are the ingredients in Luliconazole Cream?

Active ingredient: luliconazole

Inactive ingredients: benzyl alcohol, butylated hydroxytoluene, cetostearyl alcohol, isopropyl myristate, medium-chain triglycerides, methylparaben, polysorbate 60, propylene glycol, purified water, sorbitan monostearate.

Distributed by:

Oceanside Pharmaceuticals, a division of

Bausch Health US, LLC

Bridgewater, NJ 08807 USA

Manufactured by:

Bausch Health Companies Inc.

Laval, Quebec H7L 4A8, Canada

U.S. Patent Numbers: 8,980,931; 9,012,484;

9,199,977 and 9,453,006

© 2020 Bausch Health Companies Inc. or its affiliates

For more information, call 1-800-321-4576.

This Patient Information has been approved by the U.S. Food and Drug Administration.

Revised: 04/2020

9616403

Click or tap here to enter text.

NDC 68682-850-60
Rx only

LULICONAZOLE CREAM
1%

For Topical Use Only
Not for ophthalmic, oral, or intravaginal use
Keep Out of Reach of Children

Net. Wt. 60 g

OCEANSIDE
PHARMACEUTICALS